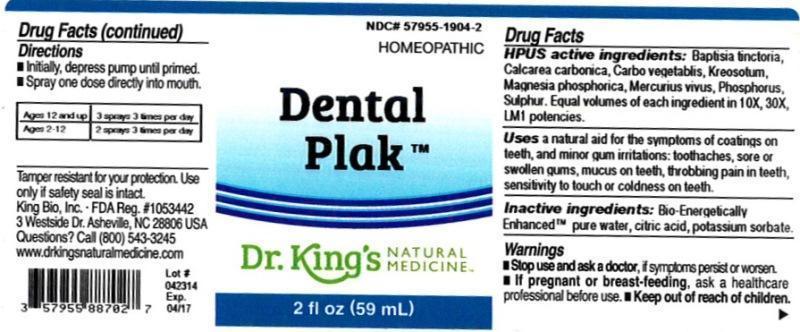 DRUG LABEL: Dental Plak
NDC: 57955-1904 | Form: LIQUID
Manufacturer: King Bio Inc.
Category: homeopathic | Type: HUMAN OTC DRUG LABEL
Date: 20140505

ACTIVE INGREDIENTS: BAPTISIA TINCTORIA ROOT 10 1/59 mL; OYSTER SHELL CALCIUM CARBONATE, CRUDE 10 [hp_X]/59 mL; ACTIVATED CHARCOAL 10 [hp_X]/59 mL; WOOD CREOSOTE 10 [hp_X]/59 mL; MAGNESIUM PHOSPHATE, DIBASIC TRIHYDRATE 10 [hp_X]/59 mL; MERCURY 10 [hp_X]/59 mL; PHOSPHORUS 10 [hp_X]/59 mL; SULFUR 10 [hp_X]/59 mL
INACTIVE INGREDIENTS: WATER; CITRIC ACID MONOHYDRATE; POTASSIUM SORBATE

Dental Plak™

ACTIVE INGREDIENT

Drug Facts__________________________________________________________________________________________________________

HPUS activeingredients: Baptisia tinctoria, Calcarea carbonica, Carbo vegetabilis, Kreosotum, Magnesia phosphorica, Mercurius vivus, Phosphorus, Sulphur. Equal volumes of each ingredient in 10X, 30X, LM1 potencies.

INDICATIONS AND USAGE

Uses a natural aid for the symptoms of coatings on teeth, and minor gum irritations: toothaches, sore or swollen gums, mucus on teeth, throbbing pain in teeth, sensitivity to touch or coldness on teeth.

Inactive Ingredients:

Bio-Energetically Enhanced™ pure water, citric acid and potassium sorbate.

Warnings

- Stop use and ask your doctor if symptoms persist or worsen.
- If pregnant or breast-feeding, ask a healthcare professional before use.

- Keep out of reach of children.

Directions

- Initially, depress pump until primed.
- Spray one dose directly into mouth.
- Ages 12 and up: 3 sprays 3 times per day.
- Ages 2-12: 2 sprays 3 times per day

OTHER SAFETY INFORMATION

Tamper resistant for your protection. Use only if safety seal is intact.

PURPOSE

Uses a natural aid for the symptoms of coatings on teeth, and minor gum irritations:

- toothaches
- sore or swollen gums
- mucus on teeth
- throbbing pain in teeth
- sensitivity to touch or coldness on teeth